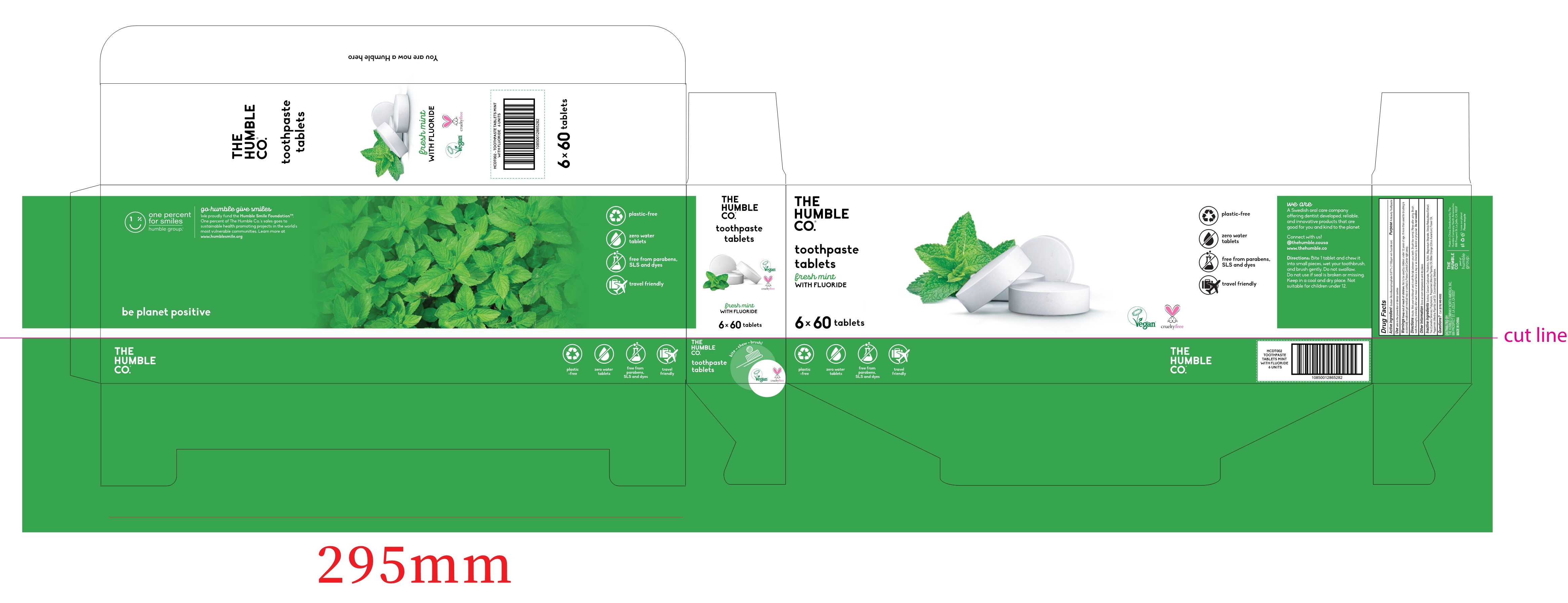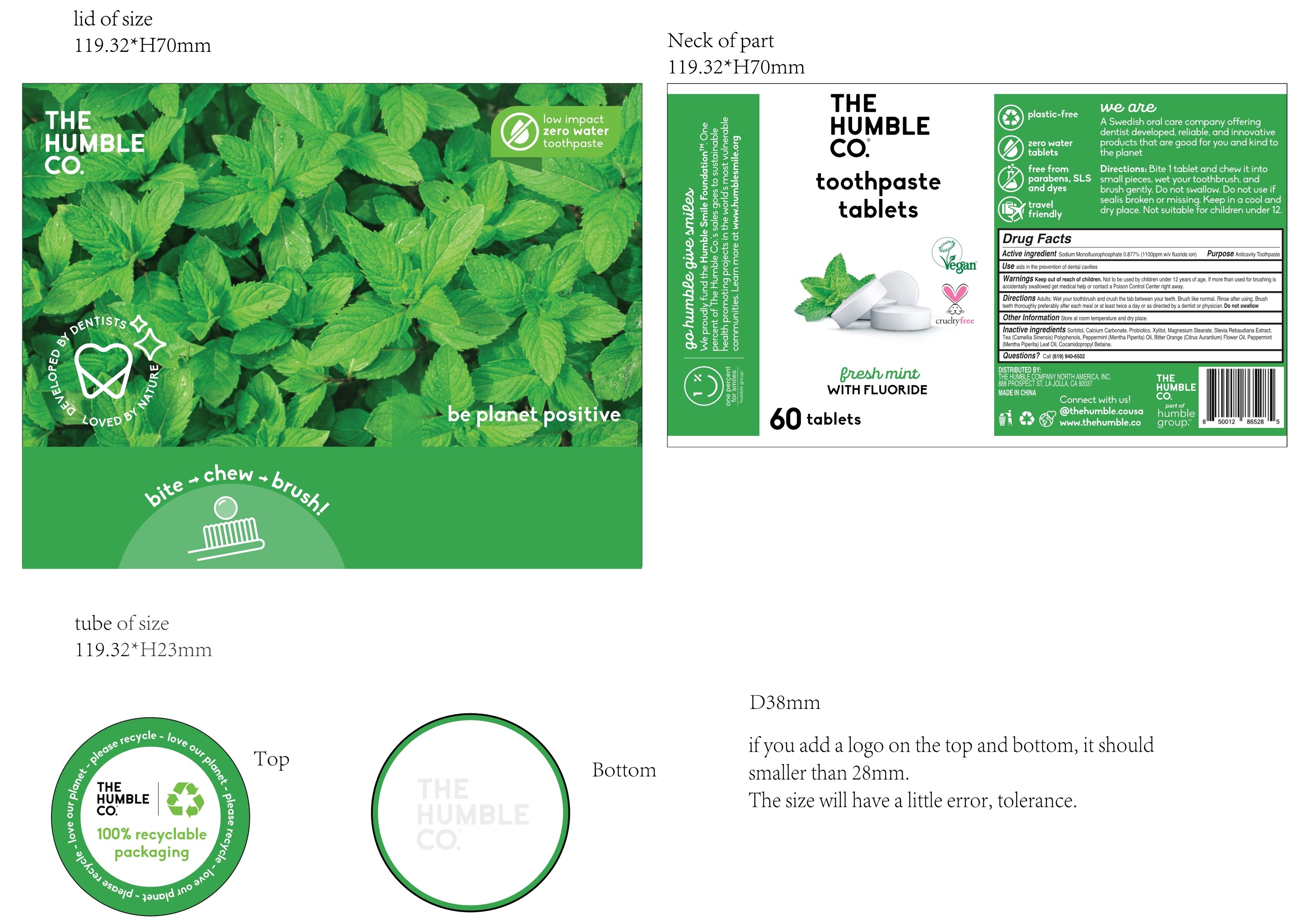 DRUG LABEL: toothpastetablets
NDC: 83525-001 | Form: TABLET
Manufacturer: HONG KONG DAILYGREEN TRADE CO., LIMITED
Category: otc | Type: HUMAN OTC DRUG LABEL
Date: 20230609

ACTIVE INGREDIENTS: SODIUM MONOFLUOROPHOSPHATE 0.877 g/100 1
INACTIVE INGREDIENTS: SORBITOL; XYLITOL; CAMELLIA SINENSIS WHOLE; MAGNESIUM STEARATE; STEVIA REBAUDIANA WHOLE; COCO/OLEAMIDOPROPYL BETAINE; CALCIUM CARBONATE; HEDEOMA PULEGIOIDES LEAF OIL; CITRUS AURANTIUM FLOWER OIL; MENTHA SPICATA OIL

83525-001
Toothpaste Tablets

Active ingredient

Sodium Monofluorophosphate 0.877% (1100ppm w/v fluoride ion)

Purpose

Anticavity Toothpaste

Use

aids in the prevention of dental cavities

Warnings

Keep out of reach of children. Not to be used by children under 12 years of age.
If more than used for brushing is accidentally swallowed get medical help or contact a Poison Control Center right away.

DO NOT USE

Not to be used by children under 12 years of age.

WHEN USING

If more than used for brushing is accidentally swallowed get medical help or contact a Poison Control Center right away.

Keep out of reach of children.

Directions

Adults: Wet your toothbrush and crush the tab between your teeth.
Brush like normal. Rinse after using.
Brush teeth thoroughly preferably after each meal or at least twice a day or as directed by a dentist or physician. Do not swallow

Other Information

Store at room temperature and dry place.

Inactive ingredients

Sorbitol, Calcium Carbonate, Probiotics, Xylitol, Magnesium Stearate, Stevia Rebaudiana Extract,
Tea (Camellia Sinensis) Polyphenols, Peppermint (Mentha Piperita) Oil, Bitter Orange (Citrus Aurantium) Flower Oil,
Peppermint (Mentha Piperita) Leaf Oil, Cocamidopropyl Betaine.

Questions?

Call (619) 940-6502

PACKAGE LABEL

83525-001-01

83525-001-11